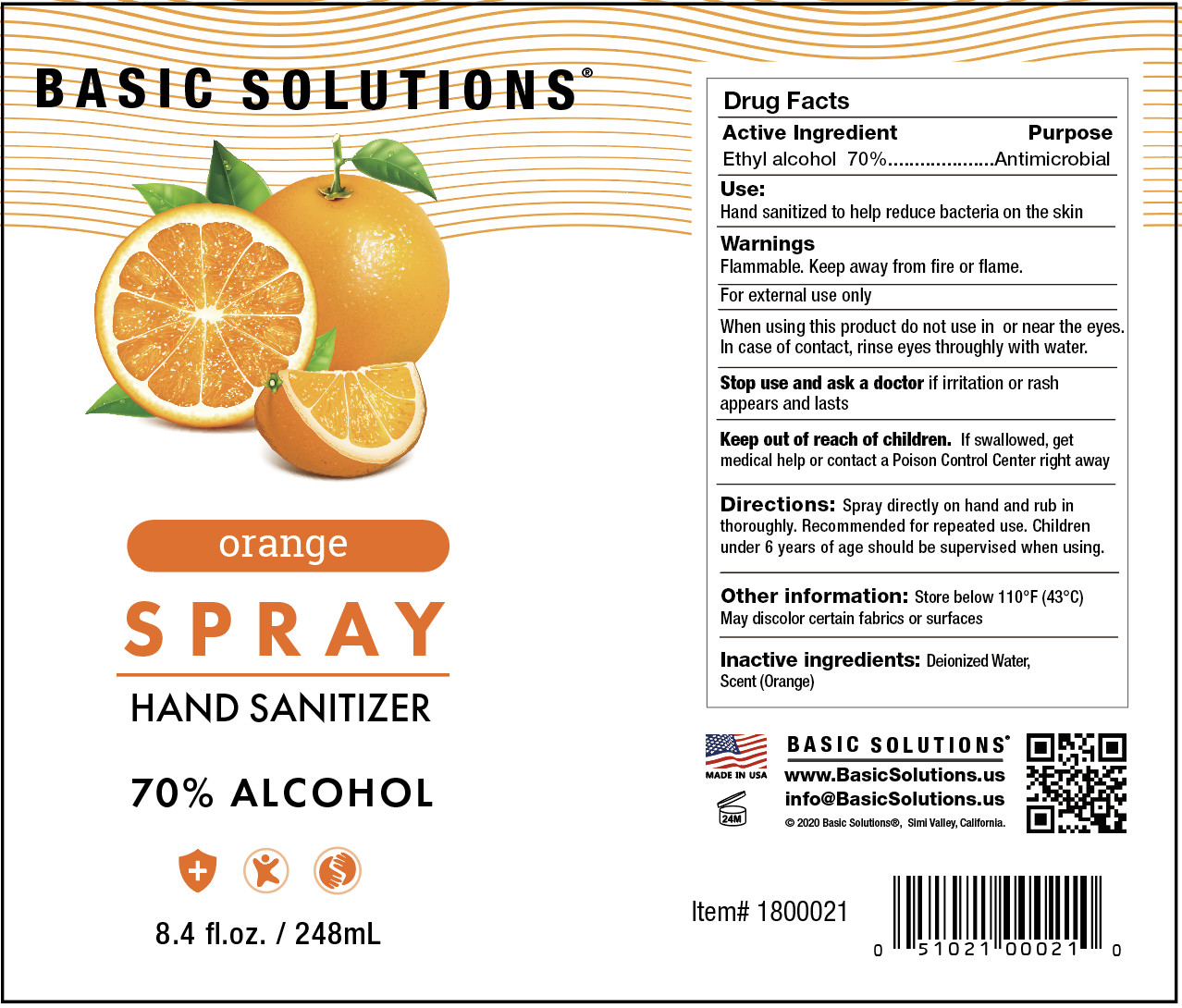 DRUG LABEL: Basic Solutions Hand sanitizerSpray 8.4 oz orange
NDC: 69797-006 | Form: SPRAY
Manufacturer: Wsm Investments, LLC Topco Sales
Category: otc | Type: HUMAN OTC DRUG LABEL
Date: 20200610

ACTIVE INGREDIENTS: ALCOHOL 173.6 mL/248 mL
INACTIVE INGREDIENTS: WATER; ORANGE

DOSAGE AND ADMINISTRATION

Store below 110°F (43°C)

INACTIVE INGREDIENT

Deionized Water、Scan（Orange）

INDICATIONS AND USAGE

Spray directly on hand and rub in thoroughly. Recommended for repeated use.

ACTIVE INGREDIENT

Ethyl alcohol

keep out of reach of children

PURPOSE

Disinfection
Sterilization
No Rinseing

WARNINGS

Flammable. Keep away from fire or flame.